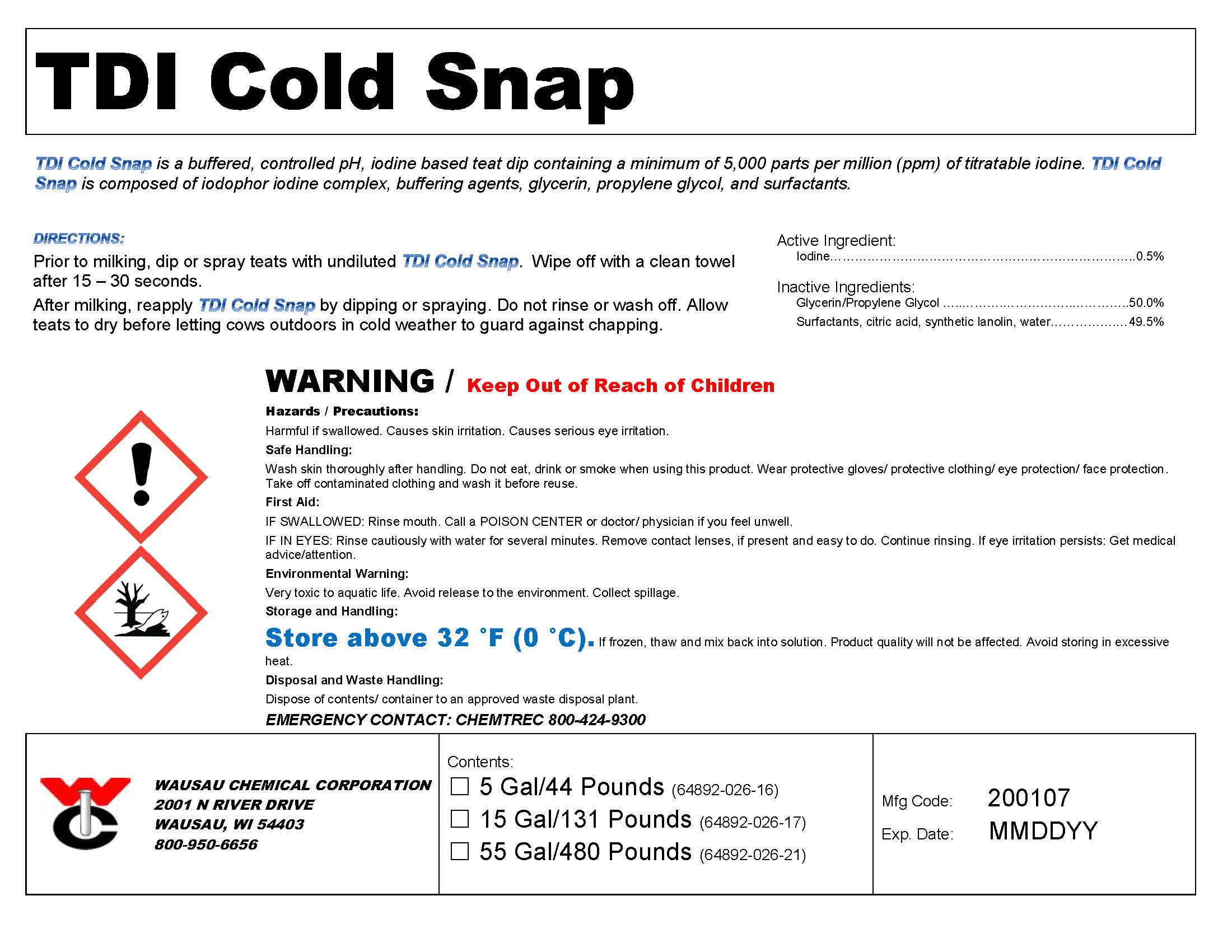 DRUG LABEL: TDI Cold Snap
NDC: 64892-026 | Form: SOLUTION
Manufacturer: Wausau Chemical
Category: animal | Type: OTC ANIMAL DRUG LABEL
Date: 20200113

ACTIVE INGREDIENTS: Iodine 5000 mg/1 L

TDI Cold Snap
Iodine Teat Dip for Winter

DISPOSAL AND WASTE HANDLING

Dispose of contents/container to an approved waste disposal plant.

ENVIRONMENTAL WARNING

Very toxic to aquatic life with long lasting effects. Avoid release to the environment. Collect spillage.

GENERAL PRECAUTIONS

WARNING / Keep Out of Reach of Children

First Aid:

IF SWALLOWED: Call a POISON CENTER or doctor/ physician if you feel unwell.
IF IN EYES: Rinse cautiously with water for several minutes. Remove contact lenses, if present and easy to do. Continue rinsing.

SAFE HANDLING WARNING

Wash skin thoroughly after handling. Do not eat, drink or smoke when using this product. Wear protective gloves/ protective clothing/ eye protection/ face protection. Take off contaminated clothing and wash it before reuse.

STORAGE AND HANDLING

Store above 32 °F (0 °C). If frozen, thaw and mix back into solution. Product quality will not be affected.

Avoid storing in excessive heat.

DIRECTIONS:

Prior to milking, dip or spray teats with undiluted TDI Cold Snap. Wipe off with a clean towel after 15 – 30 seconds.

After milking, reapply TDI Cold Snap by dipping or spraying. Do not rinse or wash off. Allow teats to dry before letting cows outdoors in cold weather to guard against chapping.

Active Ingredient:
Iodine………………………………………………………………0.5%

Wausau Chemical Corporation

2001 N River Drive

Wausau, WI 54403

800-950-6656